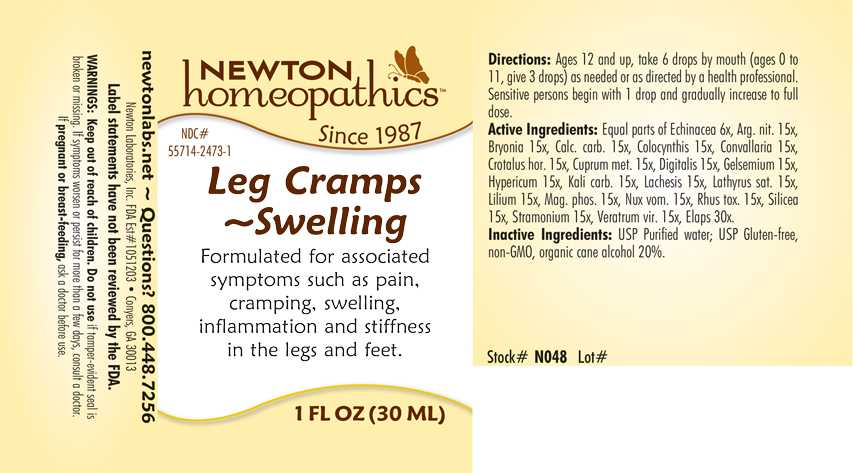 DRUG LABEL: Leg Cramps-Swelling
NDC: 55714-2473 | Form: LIQUID
Manufacturer: Newton Laboratories, Inc.
Category: homeopathic | Type: HUMAN OTC DRUG LABEL
Date: 20250207

ACTIVE INGREDIENTS: ECHINACEA, UNSPECIFIED 6 [hp_X]/1 mL; BRYONIA ALBA ROOT 15 [hp_X]/1 mL; OYSTER SHELL CALCIUM CARBONATE, CRUDE 15 [hp_X]/1 mL; CITRULLUS COLOCYNTHIS FRUIT PULP 15 [hp_X]/1 mL; CONVALLARIA MAJALIS 15 [hp_X]/1 mL; CROTALUS HORRIDUS HORRIDUS VENOM 15 [hp_X]/1 mL; COPPER 15 [hp_X]/1 mL; DIGITALIS 15 [hp_X]/1 mL; GELSEMIUM SEMPERVIRENS ROOT 15 [hp_X]/1 mL; HYPERICUM PERFORATUM 15 [hp_X]/1 mL; POTASSIUM CARBONATE 15 [hp_X]/1 mL; LACHESIS MUTA VENOM 15 [hp_X]/1 mL; LATHYRUS SATIVAS SEED 15 [hp_X]/1 mL; LILIUM LANCIFOLIUM WHOLE FLOWERING 15 [hp_X]/1 mL; MAGNESIUM PHOSPHATE, DIBASIC TRIHYDRATE 15 [hp_X]/1 mL; STRYCHNOS NUX-VOMICA SEED 15 [hp_X]/1 mL; TOXICODENDRON PUBESCENS LEAF 15 [hp_X]/1 mL; SILICON DIOXIDE 15 [hp_X]/1 mL; DATURA STRAMONIUM 15 [hp_X]/1 mL; VERATRUM VIRIDE ROOT 15 [hp_X]/1 mL; MICRURUS CORALLINUS VENOM 30 [hp_X]/1 mL; SILVER NITRATE 15 [hp_X]/1 mL
INACTIVE INGREDIENTS: ALCOHOL; WATER

Leg 2473L

INDICATIONS & USAGE SECTION

Formulated for associated symptoms such as pain, cramping, swelling, inflammation and stiffness in the legs and feet.

DOSAGE & ADMINISTRATION SECTION

Directions: Ages 12 and up, take 6 drops by mouth (ages 0 to 11, give 3 drops) as needed or as directed by a health professional. Sensitive persons begin with 1 drop and gradually increase to full dose.

OTC - ACTIVE INGREDIENT SECTION

Equal parts of Echinacea 6x, Argentum nitricum15x, Bryonia 15x, Calcarea carbonica 15x, Colocynthis 15x, Convallaria majalis 15x, Crotalus horridus 15x, Cuprum metallicum 15x, Digitalis purpurea 15x, Gelsemium sempervirens 15x, Hypericum perforatum 15x, Kali carbonicum 15x, Lachesis mutus 15x, Lathyrus sativus 15x, Lilium tigrinum 15x, Magnesia phosphorica 15x, Nux vomica 15x, Rhus toxicodendron 15x, Silicea 15x, Stramonium 15x, Veratrum viride 15x, Elaps corallinus 30x.

OTC - PURPOSE SECTION

Formulated for associated symptoms such as pain, cramping, swelling, inflammation and stiffness in the legs and feet.

INACTIVE INGREDIENT SECTION

Inactive Ingredients: USP Purified Water; USP Gluten-free, non-GMO, organic cane alcohol 20%.

QUESTIONS SECTION

newtonlabs.net – Questions? 800.448.7256

Newton Laboratories, Inc. FDA Est # 1051203 - Conyers, GA 30013

WARNINGS SECTION

WARNINGS: Keep out of reach of children. Do not use if tamper-evident seal is broken or missing. If symptoms worsen or persist for more than a few days, consult a doctor. If pregnant or breast-feeding, ask a doctor before use.

OTC - PREGNANCY OR BREAST FEEDING SECTION

If pregnant or breast-feeding, ask a doctor before use.

OTC - KEEP OUT OF REACH OF CHILDREN SECTION

Keep out of reach of children.